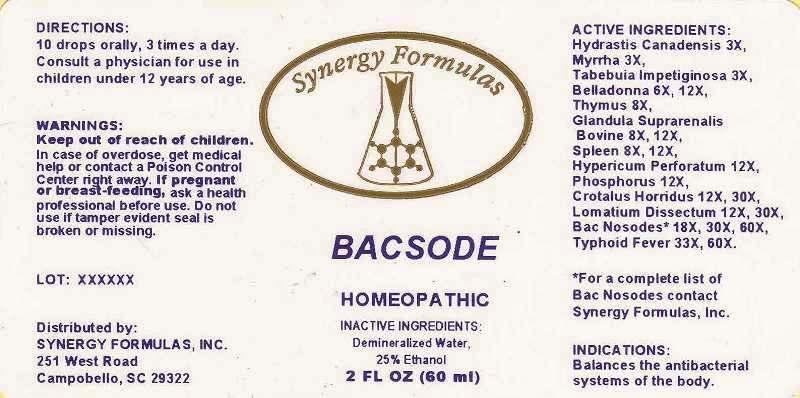 DRUG LABEL: Bacsode
NDC: 43772-0020 | Form: LIQUID
Manufacturer: Synergy Formulas
Category: homeopathic | Type: HUMAN OTC DRUG LABEL
Date: 20130827

ACTIVE INGREDIENTS: GOLDENSEAL 3 [hp_X]/1 mL; MYRRH 3 [hp_X]/1 mL; TABEBUIA IMPETIGINOSA BARK 3 [hp_X]/1 mL; ATROPA BELLADONNA 6 [hp_X]/1 mL; BOS TAURUS THYMUS 8 [hp_X]/1 mL; BOS TAURUS ADRENAL GLAND 8 [hp_X]/1 mL; BOS TAURUS SPLEEN 8 [hp_X]/1 mL; HYPERICUM PERFORATUM 12 [hp_X]/1 mL; PHOSPHORUS 12 1/1 mL; CROTALUS HORRIDUS HORRIDUS VENOM 12 [hp_X]/1 mL; LOMATIUM DISSECTUM ROOT 12 [hp_X]/1 mL; BOTULINUM TOXIN TYPE A 18 [hp_X]/1 mL; CHLAMYDIA TRACHOMATIS 18 [hp_X]/1 mL; CLOSTRIDIUM TETANI 18 [hp_X]/1 mL; ESCHERICHIA COLI 18 [hp_X]/1 mL; NEISSERIA MENINGITIDIS 18 [hp_X]/1 mL; PASTEURELLA MULTOCIDA 18 [hp_X]/1 mL; STREPTOCOCCUS PNEUMONIAE 18 [hp_X]/1 mL; PROTEUS VULGARIS 18 [hp_X]/1 mL; PSEUDOMONAS AERUGINOSA 18 [hp_X]/1 mL; STAPHYLOCOCCUS AUREUS 18 [hp_X]/1 mL; SALMONELLA ENTERICA SUBSP. ENTERICA SEROVAR TYPHI 33 [hp_X]/1 mL
INACTIVE INGREDIENTS: WATER; ALCOHOL

Drug Facts:

ACTIVE INGREDIENTS:

Hydrastis Canadensis 3X, Myrrha 3X, Tabebuia Impetiginosa 3X, Belladonna 6X, 12X, Thymus (Bovine) 8X, Glandula Suprarenalis Bovinum 8X, 12X, Spleen (Bovine) 8X, 12X, Hypericum Perforatum 12X, Phosphorus 12X, Crotalus Horridus 12X, 30X, Lomatium Dissectum 12X, 30X, Botulinum 18X, 30X, 60X, Chlamydia Trachomatis 18X, 30X, 60X, Clostridium Tetani (Tetanus) 18X, 30X, 60X, Escherichia Coli 18X, 30X, 60X, Meningococcinum 18X, 30X, 60X, Pasteurellosis Nosode 18X, 30X, 60X, Pneumococcus 18X, 30X, 60X, Proteus (Vulgaris) 18X, 30X, 60X, Pseudomonas Aeruginosa 18X, 30X, 60X, Staphylococcus Aureus 18X, 30X, 60X, Typhoid Fever 33X, 60X

INDICATIONS:

Balances the antibacterial systems of the body.

WARNINGS:

Keep out of reach of children. In case of overdose, get medical help or contact a Poison Control Center right away.

If pregnant or breast-feeding, ask a health professional before use.

Do not use if tamper evident seal is broken or missing.

Keep out of reach of children. In case of overdose, get medical help or contact a Poison Control Center right away.

DIRECTIONS:

10 drops orally, 3 times a day. Consult a physician for use in children under 12 years of age.

INDICATIONS:

Balances the antibacterial systems of the body.

INACTIVE INGREDIENTS:

Demineralized Water, 25% Ethanol

QUESTIONS:

Distributed by:

SYNERGY FORMULAS, INC.

251 West Road

Campobello, SC 29322

*For complete list of Bac Nosodes contact Synergy Formulas, Inc.

PACKAGE DISPLAY LABEL:

Synergy Formulas

BACSODE

HOMEOPATHIC

2 FL OZ (60 mL)